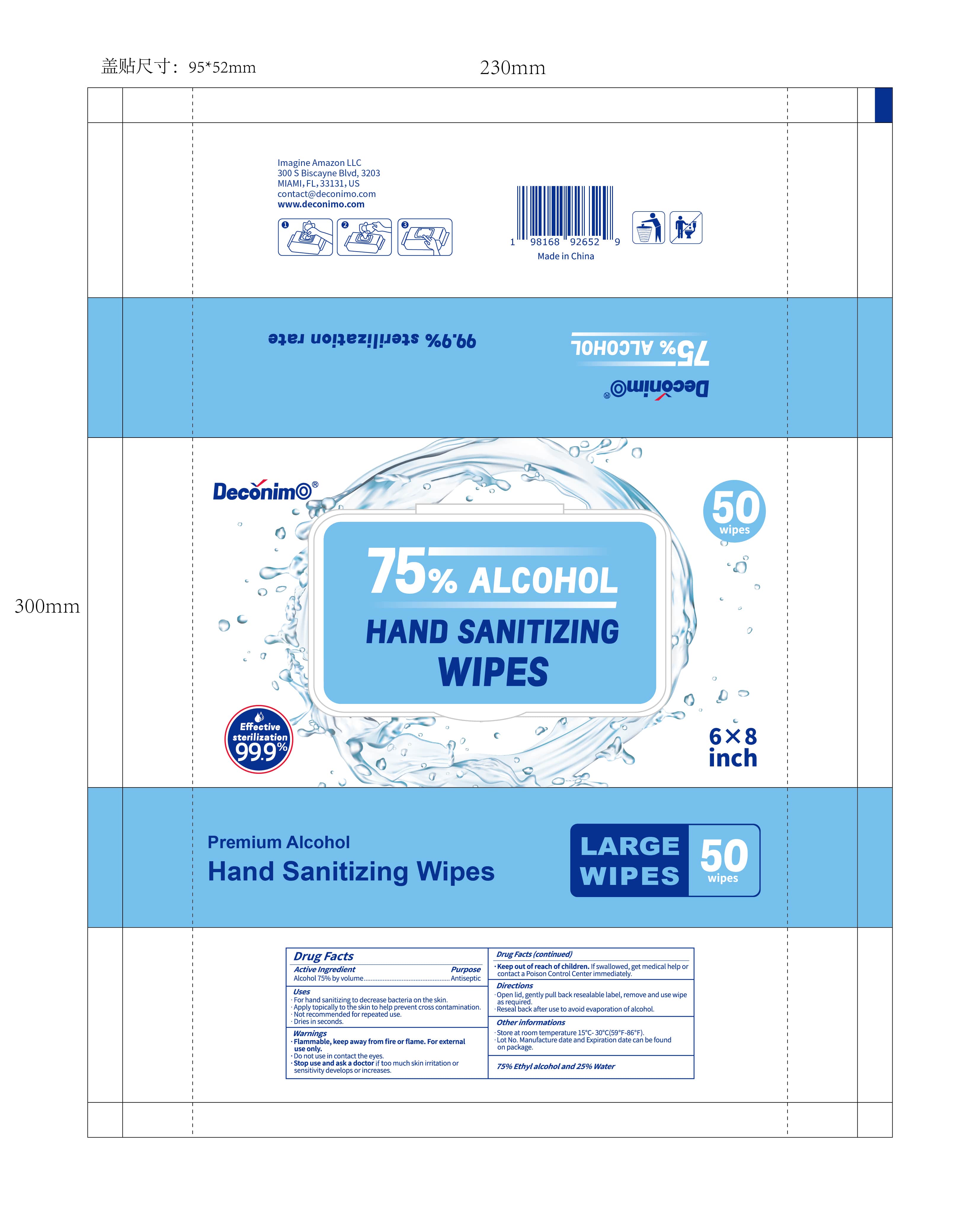 DRUG LABEL: Deconimo
NDC: 85380-0002 | Form: CLOTH
Manufacturer: IMAGINE AMAZON LLC
Category: otc | Type: HUMAN OTC DRUG LABEL
Date: 20250401

ACTIVE INGREDIENTS: ALCOHOL 75 mL/100 mL
INACTIVE INGREDIENTS: WATER

Uses
For hand sanitizing to decrease bacteria on the skin.
Purpose .Antiseptic
Apply topically to the skin to help prevent cross contamination. Not recommended for repeated use.

Warnings
• Flammable, keep away from fire or flame. For external use only.
• Do not use in contact the eyes.
Stop use and ask a doctor if too much skin irritation or
sensitivity develops or increases.
• Keep out of reach of children. If swallowed, get medical help or contact a Poison Control Center immediately.

INACTIVE INGREDIENT

Water

Directions
Open lid, gently pull back resealable label, remove and use wipe as required.
•Reseal back after use to avoid evaporation of alcohol.
Other informations
• Store at room temperature 15°C-30°C(59°F-86°F).
Lot No. Manufacture date and Expiration date can be found on package.

Active Ingredient
Alcohol 75% by volume

Keep out of reach of children. If swallowed, get medical help or contact a Poison Control Center immediately.
Directions

Uses
For hand sanitizing to decrease bacteria on the skin.
Purpose .Antiseptic
Apply topically to the skin to help prevent cross contamination. Not recommended for repeated use.

PACKAGE LABEL

Deconimo
75% ALCOHOL
HAND SANITIZING WIPES
50
wipes
Effective sterilization
99.9%
Premium Alcohol
Hand Sanitizing Wipes
Drug Facts
Drug Facts (continued)
6X8 inch
LARGE 50
WIPES wipes
I
Active Ingredient
Alcohol 75% by volume...
Uses
For hand sanitizing to decrease bacteria on the skin.
Purpose .Antiseptic
Apply topically to the skin to help prevent cross contamination. Not recommended for repeated use.
⚫ Dries in seconds.
Warnings
• Flammable, keep away from fire or flame. For external use only.
• Do not use in contact the eyes.
Stop use and ask a doctor if too much skin irritation or
sensitivity develops or increases.
• Keep out of reach of children. If swallowed, get medical help or contact a Poison Control Center immediately.
Directions
Open lid, gently pull back resealable label, remove and use wipe as required.
•Reseal back after use to avoid evaporation of alcohol.
Other informations
• Store at room temperature 15°C-30°C(59°F-86°F).
Lot No. Manufacture date and Expiration date can be found on package.
75% Ethyl alcohol and 25% Water
|
I
|
I